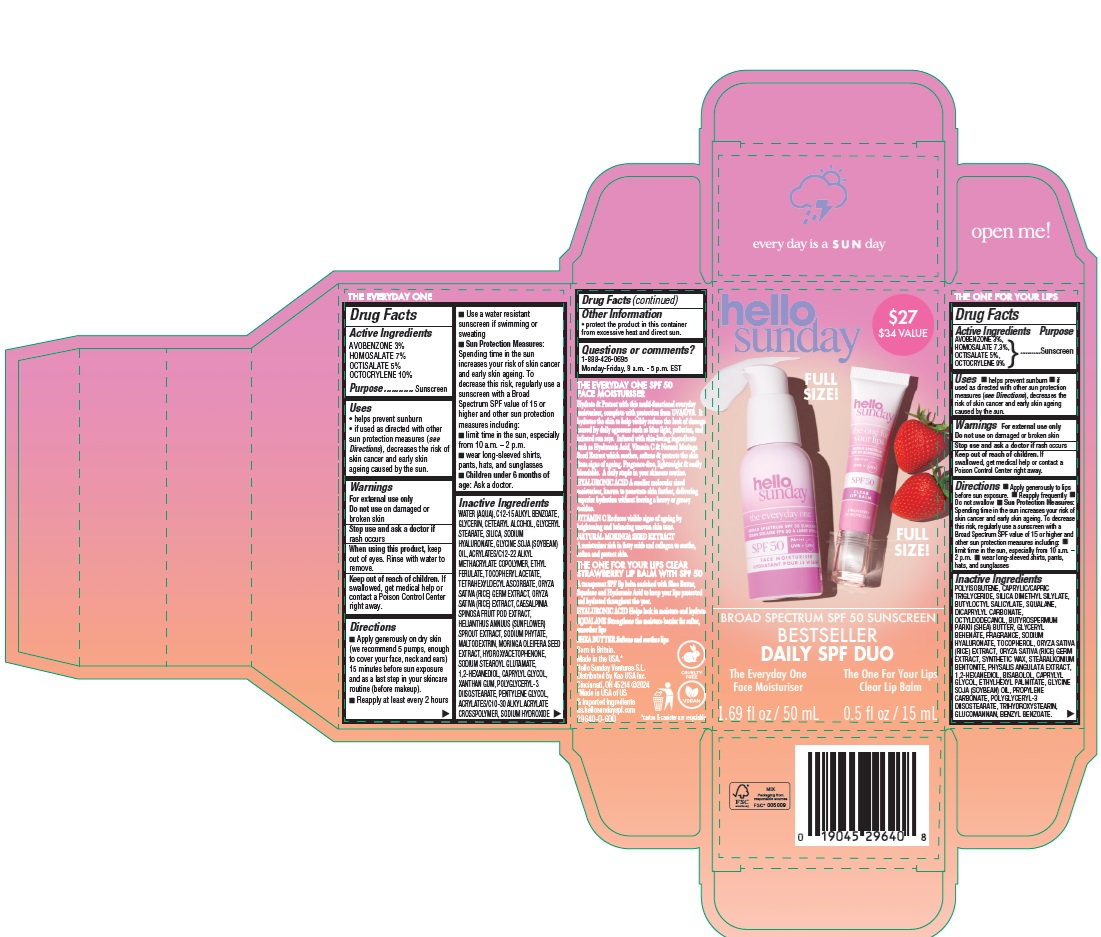 DRUG LABEL: Hello Sunday Bestseller Daily SPF Duo
NDC: 10596-003 | Form: KIT | Route: TOPICAL
Manufacturer: Kao USA Inc.
Category: otc | Type: HUMAN OTC DRUG LABEL
Date: 20250131

ACTIVE INGREDIENTS: HOMOSALATE 70 mg/1 mL; OCTOCRYLENE 100 mg/1 mL; OCTISALATE 50 mg/1 mL; AVOBENZONE 30 mg/1 mL; HOMOSALATE 73 mg/1 mL; AVOBENZONE 30 mg/1 mL; OCTISALATE 50 mg/1 mL; OCTOCRYLENE 90 mg/1 mL
INACTIVE INGREDIENTS: SODIUM STEAROYL GLUTAMATE; ACRYLATES/C10-30 ALKYL ACRYLATE CROSSPOLYMER (60000 MPA.S); HELIANTHUS ANNUUS SPROUT; SODIUM HYDROXIDE; SOYBEAN OIL; RICE GERM; WATER; PHYTATE SODIUM; 1,2-HEXANEDIOL; GLYCERYL MONOSTEARATE; MALTODEXTRIN; GLYCERIN; POLYGLYCERYL-3 DIISOSTEARATE; SILICON DIOXIDE; HYDROXYACETOPHENONE; XANTHAN GUM; .ALPHA.-TOCOPHEROL ACETATE; ALKYL (C12-15) BENZOATE; MORINGA OLEIFERA SEED; ETHYL FERULATE; CAESALPINIA SPINOSA FRUIT POD; CAPRYLYL GLYCOL; PENTYLENE GLYCOL; CETOSTEARYL ALCOHOL; HYALURONATE SODIUM; TETRAHEXYLDECYL ASCORBATE; BUTYLOCTYL SALICYLATE; OCTYLDODECANOL; ETHYLHEXYL PALMITATE; CAPRYLYL GLYCOL; SYNTHETIC WAX (1200 MW); SOYBEAN OIL; KONJAC MANNAN; POLYISOBUTYLENE (1300 MW); TRIHYDROXYSTEARIN; HYALURONATE SODIUM; RICE GERM; SHEA BUTTER; PROPYLENE CARBONATE; SILICON DIOXIDE; POLYGLYCERYL-3 DIISOSTEARATE; DICAPRYLYL CARBONATE; GLYCERYL MONOBEHENATE; 1,2-HEXANEDIOL; PHYSALIS ANGULATA WHOLE; BENZYL BENZOATE; SILICA DIMETHYL SILYLATE; SQUALANE; TOCOPHEROL; MEDIUM-CHAIN TRIGLYCERIDES; LEVOMENOL

Hello Sunday Bestseller Daily SPF Duo

Active Ingredients

THE ONE FOR YOUR LIPS

AVOBENZONE 3%
HOMOSALATE 7.3%
OCTISALATE 5%
OCTOCRYLENE 9%

THE EVERYDAY ONE

AVOBENZONE 3%
HOMOSALATE 7%
OCTISALATE 5%
OCTOCRYLENE 10%

Purpose

Sunscreen

Uses

- helps prevent sunburn
- if used as directed with other sun protection measures (see Directions), decreases the risk of skin cancer and early skin ageing caused by the sun.

Warnings

For external use only

Do not use

on damaged or broken skin

Stop use and ask a doctor if

rash occurs

When using this product

keep out of eyes. Rinse with water to remove.

Keep out of reach of children.

If swallowed, get medical help or contact a Poison Control Center right away.

Directions

THE ONE FOR YOUR LIPS

- Apply generously to lips before sun exposure.
- Reapply frequently
- Do not swallow
- Sun Protection Measures: Spending time in the sun increases your risk of skin cancer and early skin ageing. To decrease this risk, regularly use a sunscreen with a Broad Spectrum SPF value of 15 or higher and other sun protection measures including:
- limit time in the sun, especially from 10 a.m. – 2 p.m.
- wear long-sleeved shirts, pants, hats, and sunglasses

THE EVERYDAY ONE

- Apply generously on dry skin (we recommend 5 pumps, enough to cover your face, neck and ears) 15 minutes before sun exposure and as a last step in your skincare routine (before makeup).
- Reapply at least every 2 hours
- Use a water resistant sunscreen if swimming or sweating
- Sun Protection Measures: Spending time in the sun increases your risk of skin cancer and early skin ageing. To decrease this risk, regularly use a sunscreen with a Broad Spectrum SPF value of 15 or higher and other sun protection measures including:
- limit time in the sun, especially from 10 a.m. – 2 p.m.
- wear long-sleeved shirts, pants, hats, and sunglasses
- Children under 6 months of age: Ask a doctor

Inactive Ingredients

THE ONE FOR YOUR LIPS

POLYISOBUTENE, CAPRYLIC/CAPRIC TRIGLYCERIDE, SILICA DIMETHYL SILYLATE, BUTYLOCTYL SALICYLATE, SQUALANE, DICAPRYLYL CARBONATE, OCTYLDODECANOL, BUTYROSPERMUM PARKII (SHEA) BUTTER, GLYCERYL BEHENATE, FRAGRANCE, SODIUM HYALURONATE, TOCOPHEROL, ORYZA SATIVA (RICE) EXTRACT, ORYZA SATIVA (RICE) GERM EXTRACT, SYNTHETIC WAX, STEARALKONIUM BENTONITE, PHYSALIS ANGULATA EXTRACT, 1,2-HEXANEDIOL, BISABOLOL, CAPRYLYL GLYCOL, ETHYLHEXYL PALMITATE, GLYCINE SOJA (SOYBEAN) OIL, PROPYLENE CARBONATE, POLYGLYCERYL-3 DIISOSTEARATE, TRIHYDROXYSTEARIN, GLUCOMANNAN, BENZYL BENZOATE.

THE EVERYDAY ONE

WATER (AQUA), C12-15 ALKYL BENZOATE, GLYCERIN, CETEARYL ALCOHOL, GLYCERYL STEARATE, SILICA, SODIUM HYALURONATE, GLYCINE SOJA (SOYBEAN) OIL, ACRYLATES/C12-22 ALKYL METHACRYLATE COPOLYMER, ETHYL FERULATE, TOCOPHERYL ACETATE, TETRAHEXYLDECYL ASCORBATE, ORYZA SATIVA (RICE) GERM EXTRACT, ORYZA SATIVA (RICE) EXTRACT, CAESALPINIA SPINOSA FRUIT POD EXTRACT, HELIANTHUS ANNUUS (SUNFLOWER) SPROUT EXTRACT, SODIUM PHYTATE, MALTODEXTRIN, MORINGA OLEIFERA SEED EXTRACT, HYDROXYACETOPHENONE, SODIUM STEAROYL GLUTAMATE, 1,2-HEXANEDIOL, CAPRYLYL GLYCOL, XANTHAN GUM, POLYGLYCERYL-3 DIISOSTEARATE, PENTYLENE GLYCOL, ACRYLATES/C10-30 ALKYL ACRYLATE CROSSPOLYMER, SODIUM HYDROXIDE

Other Information

- protect the product in this container from excessive heat and direct sun.

Questions or comments?

1-888-426-0695
Monday-Friday, 9 a.m. - 5 p.m. EST